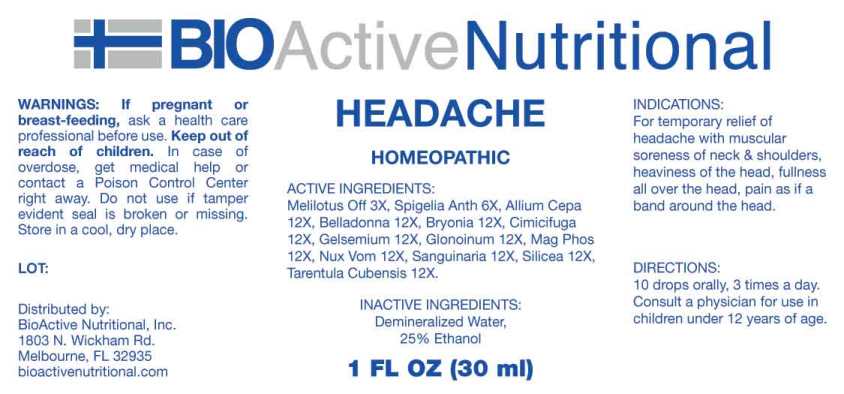 DRUG LABEL: Headache
NDC: 43857-0488 | Form: LIQUID
Manufacturer: BioActive Nutritionals, Inc.
Category: homeopathic | Type: HUMAN OTC DRUG LABEL
Date: 20241017

ACTIVE INGREDIENTS: MELILOTUS OFFICINALIS TOP 3 [hp_X]/1 mL; SPIGELIA ANTHELMIA WHOLE 6 [hp_X]/1 mL; ONION 12 [hp_X]/1 mL; ATROPA BELLADONNA 12 [hp_X]/1 mL; BRYONIA ALBA ROOT 12 [hp_X]/1 mL; BLACK COHOSH 12 [hp_X]/1 mL; GELSEMIUM SEMPERVIRENS ROOT 12 [hp_X]/1 mL; NITROGLYCERIN 12 [hp_X]/1 mL; MAGNESIUM PHOSPHATE, DIBASIC TRIHYDRATE 12 [hp_X]/1 mL; STRYCHNOS NUX-VOMICA SEED 12 [hp_X]/1 mL; SANGUINARIA CANADENSIS ROOT 12 [hp_X]/1 mL; SILICON DIOXIDE 12 [hp_X]/1 mL; CITHARACANTHUS SPINICRUS 12 [hp_X]/1 mL
INACTIVE INGREDIENTS: WATER; ALCOHOL

DRUG FACTS:

ACTIVE INGREDIENTS:

Melilotus Officinalis 3X, Spigelia Anthelmia 6X, Allium Cepa 12X, Belladonna 12X, Bryonia (Alba) 12X, Cimicifuga Racemosa 12X, Gelsemium Sempervirens 12X, Glonoinum 12X, Magnesia Phosphorica 12X, Nux Vomica 12X, Sanguinaria Canadensis 12X, Silicea 12X, Tarentula Cubensis 12X.

INDICATIONS:

For temporary relief of headache with muscular soreness of neck and shoulders, heaviness of the head, fullness all over the head, pain as if a band around the head.

WARNINGS:

If pregnant or breast-feeding, ask a health care professional before use.

Keep out of reach of children. In case of overdose, get medical help or contact a Poison Control Center right away.

Do not use if tamper evident seal is broken or missing.

Store in a cool, dry place.

Keep out of reach of children. In case of overdose, get medical help or contact a Poison Control Center right away.

DIRECTIONS:

10 drops orally, 3 times a day. Consult a physician for use in children under 12 years of age.

INDICATIONS:

For temporary relief of headache with muscular soreness of neck and shoulders, heaviness of the head, fullness all over the head, pain as if a band around the head.

INACTIVE INGREDIENTS:

Demineralized Water, 25% Ethanol

QUESTIONS:

Distributed by:
BioActive Nutritional, Inc.
1803 N. Wickham Rd.
Melbourne, FL 32935
bioactivenutritional.com

PACKAGE LABEL DISPLAY:

BIOActive Nutritional

HEADACHE

HOMEOPATHIC

1 FL OZ (30 ml)